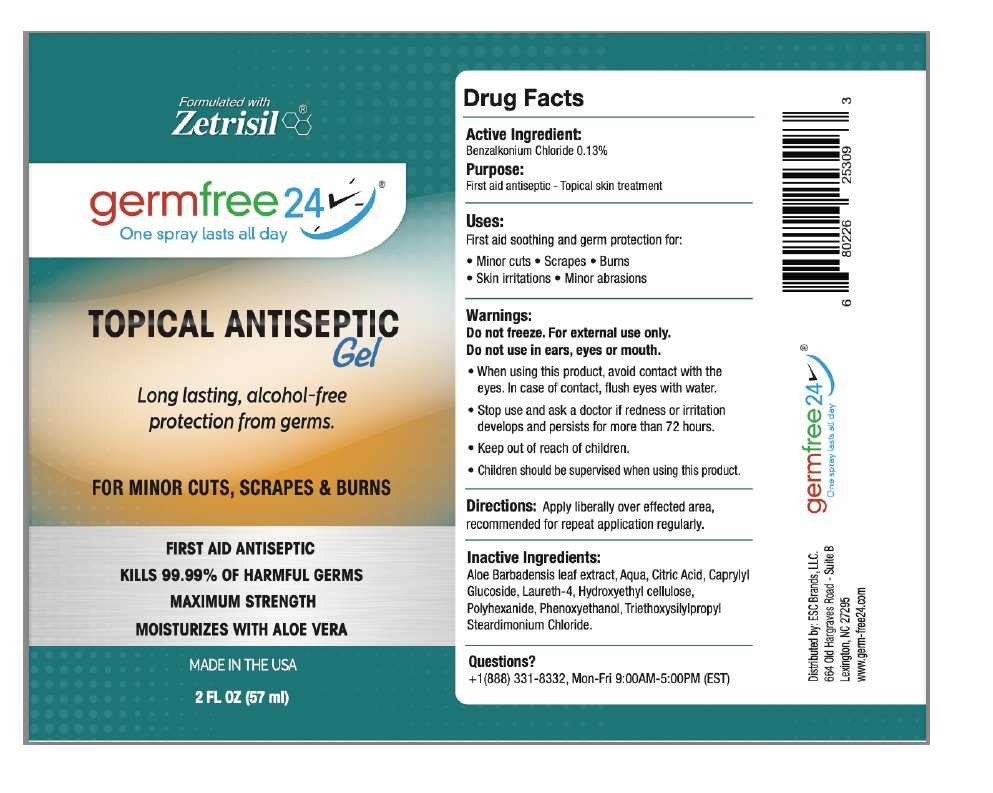 DRUG LABEL: Germ Free Topical Antiseptic
NDC: 71884-008 | Form: GEL
Manufacturer: Enviro Specialty Chemicals Inc
Category: otc | Type: HUMAN OTC DRUG LABEL
Date: 20241231

ACTIVE INGREDIENTS: BENZALKONIUM CHLORIDE 1.3 mg/1 mL
INACTIVE INGREDIENTS: ALOE VERA LEAF; WATER; CITRIC ACID MONOHYDRATE; CAPRYLYL GLUCOSIDE; LAURETH-4; HYDROXYETHYL CELLULOSE, UNSPECIFIED; POLIHEXANIDE; PHENOXYETHANOL; TRIETHOXYSILYLPROPYL STEARDIMONIUM CHLORIDE

germfree 24® Topical Antiseptic Gel

Active Ingredient:

Benzalkonium Chloride 0.13%

Purpose:

First aid antiseptic - Topical skin treatment

Uses:

First aid soothing and germ protection for:

• Minor cuts • Scrapes • Burns • Skin irritations • Minor abrasions

Warnings:

Do not freeze. For external use only.

Do not use in ears, eyes or mouth.

• When using this product, avoid contact with the eyes. In case of contact, flush eyes with water.

• Stop use and ask a doctor if redness or irritation develops and persists for more than 72 hours.

• Keep out of reach of children.

• Children should be supervised when using this product.

Directions:

Apply liberally over affected area, recommended for repeat application regularly.

Inactive Ingredients:

Aloe Barbadenis leaf extract, Aqua, Citric Acid, Caprylyl Glucoside, Laureth-4, Hydroxyethyl cellulose, Polyhexanide, Phenoxyethanol, Triethoxysilylpropyl Steardimonium Chloride.

Questions?

+1(888) 331-8332, Mon-Fri 9:00AM-5:00PM (EST)

Formulated with Zetrisil®

One spray lasts all day

Long lasting, alcohol-free protection from germs.

FOR MINOR CUTS, SCRAPES & BURNS

KILLS 99.99% OF HARMFUL GERMS

MAXIMUM STRENGTH

MOISTURIZES WITH ALOE VERA

MADE IN THE USA

Distributed by: ESC Brands, LLC.

664 Old Hargraves Road - Suite B

Lexington, NC 27295

www.germ-free24.com